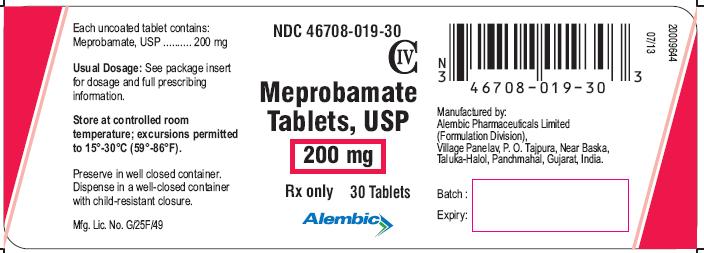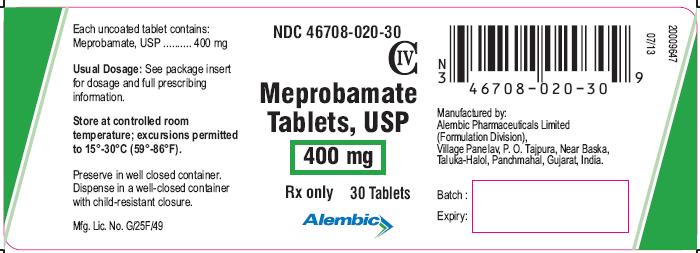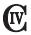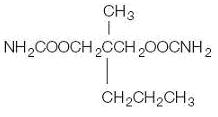 DRUG LABEL: MEPROBAMATE
NDC: 46708-019 | Form: TABLET
Manufacturer: Alembic Pharmaceuticals Limited
Category: prescription | Type: Human Prescription Drug Label
Date: 20230110
DEA Schedule: CIV

ACTIVE INGREDIENTS: MEPROBAMATE 200 mg/1 1
INACTIVE INGREDIENTS: SILICON DIOXIDE; MAGNESIUM STEARATE; CELLULOSE, MICROCRYSTALLINE; SODIUM STARCH GLYCOLATE TYPE A POTATO; STARCH, CORN

Meprobamate Tablets USP
Rx Only

DESCRIPTION

Meprobamate is a white powder with a characteristic odor and a bitter taste. It is slightly soluble in water, freely soluble in acetone and alcohol, and sparingly soluble in ether. The structural formula of meprobamate is:

C9H18N2O4 M.W. 218.25
Meprobamate Tablets USP 200 mg and 400 mg for oral administration contain the following inactive ingredients: colloidal silicon dioxide, magnesium stearate, microcrystalline cellulose, sodium starch glycolate and pregelatinised starch.

CLINICAL PHARMACOLOGY

Meprobamate is a carbamate derivative which has been shown in animal studies to have effects at multiple sites in the central nervous system including the thalamus and limbic system.

INDICATIONS & USAGE

Meprobamate tablets are indicated for the management of anxiety disorders or for the short-term relief of the symptoms of anxiety. Anxiety or tension associated with the stress of everyday life usually do not require treatment with an anxiolytic.
The effectiveness of meprobamate tablets in long-term use, that is, more than 4 months, has not been assessed by systematic clinical studies. The physician should periodically reassess the usefulness of the drug for the individual patient.

CONTRAINDICATIONS

Acute intermittent porphyria as well as allergic or idiosyncratic reactions to meprobamate or related compounds such as carisoprodol, mebutamate, tybamate, or carbromal.

WARNINGS

Drug Dependence
Physical dependence, psychological dependence, and abuse have occurred. When chronic intoxication from prolonged use occurs, it usually involves ingestion of greater than recommended doses and is manifested by ataxia, slurred speech, and vertigo.
Therefore, careful supervision of dose and amounts prescribed is advised, as well as avoidance of prolonged administration, especially for alcoholics and other patients with a known propensity for taking excessive quantities of drugs.
Sudden withdrawal of the drug after prolonged and excessive use may precipitate recurrence of pre-existing symptoms such as anxiety, anorexia, insomnia, or withdrawal reactions such as vomiting, ataxia, tremors, muscle twitching, confusional states, hallucinosis, and rarely, convulsive seizures. Such seizures are more likely to occur in persons with central nervous system damage or pre-existent or latent convulsive disorders. Onset of withdrawal symptoms occurs usually within 12 to 48 hours after discontinuation of meprobamate; symptoms usually cease within the next 12 to 48 hours.
When excessive dosage has continued for weeks or months, dosage should be reduced gradually over a period of one or two weeks rather than abruptly stopped. Alternatively, a long-acting barbiturate may be substituted, then gradually withdrawn.
Potentially Hazardous Tasks
Patients should be warned that meprobamate may impair the mental and/or physical abilities required for performance of potentially hazardous tasks such as driving or operating machinery.
Additive Effects
Since the effects of meprobamate and alcohol or meprobamate and other CNS depressants or psychotropic drugs may be additive, appropriate caution should be exercised with patients who take more than one of these agents simultaneously.
Usage in Pregnancy and Lactation
An increased risk of congenital malformations associated with the use of minor tranquilizers (meprobamate, chlordiazepoxide and diazepam) during the first trimester of pregnancy has been suggested in several studies. Because use of these drugs is rarely a matter of urgency, their use during this period should almost always be avoided. The possibility that a woman of childbearing potential may be pregnant at the time of institution of therapy should be considered. Patients should be advised that if they become pregnant during therapy or intend to become pregnant they should communicate with their physician about the desirability of discontinuing the drug.
Meprobamate passes the placental barrier. It is present both in umbilical cord blood at or near maternal plasma levels and in breast milk of lactating mothers at concentrations two to four times that of maternal plasma. When use of meprobamate is contemplated in breastfeeding patients, the drug's higher concentration in breast milk as compared to maternal plasma should be considered.
Usage in Children
Meprobamate tablets should not be administered to children under age six, since there is a lack of documented evidence for safety and effectiveness in this age group.

PRECAUTIONS

The lowest effective dose should be administered, particularly to elderly and/or debilitated patients, in order to preclude oversedation.
The possibility of suicide attempts should be considered and the least amount of drug feasible should be dispensed at any one time.
Meprobamate is metabolized in the liver and excreted by the kidney; to avoid its excess accumulation, caution should be exercised in administration to patients with compromised liver or kidney function.
Meprobamate occasionally may precipitate seizures in epileptic patients.

GERIATRIC USE

Clinical studies of meprobamate tablets did not include sufficient numbers of subjects aged 65 and over to determine whether they respond differently from younger subjects. Other reported clinical experience has not identified differences in responses between the elderly and younger patients. In general, dose selection for an elderly patient should be cautious, usually starting at the low end of the dosing range, reflecting the greater frequency of decreased hepatic, renal, or cardiac function, and of concomitant disease or other drug therapy.

ADVERSE REACTIONS

Central Nervous System
Drowsiness, ataxia, dizziness, slurred speech, headache, vertigo, weakness, paresthesias, impairment of visual accommodation, euphoria, overstimulation, paradoxical excitement, fast EEG activity.
Gastrointestinal
Nausea, vomiting, diarrhea.
Cardiovascular
Palpitation, tachycardia, various forms of arrhythmia, transient ECG changes, syncope; also hypotensive crisis (including one fatal case).
Allergic or Idiosyncratic
Allergic or idiosyncratic reactions are usually seen within the period of the first to fourth dose in patients having had no previous contact with the drug. Milder reactions are characterized by an itchy, urticarial, or erythematous maculopapular rash which may be generalized or confined to the groin. Other reactions have included leukopenia, acute nonthrombocytopenic purpura, petechiae, ecchymoses, eosinophilia, peripheral edema, adenopathy, fever, fixed drug eruption with cross
reaction to carisoprodol, and cross sensitivity between meprobamate/mebutamate and meprobamate/carbromal.
More severe hypersensitivity reactions, rarely reported, include hyperpyrexia, chills, angioneurotic edema, bronchospasm, oliguria and anuria. Also, anaphylaxis, erythema multiforme, exfoliative dermatitis, stomatitis, proctitis, Stevens-Johnson syndrome and bullous dermatitis, including one fatal case of the latter following administration of meprobamate in combination with prednisolone.
In case of allergic or idiosyncratic reactions to meprobamate, discontinue the drug and initiate appropriate symptomatic therapy, which may include epinephrine, antihistamines, and in severe cases, corticosteroids. In evaluating possible allergic reactions, also consider allergy to excipients.
Hematologic (See also Allergic or Idiosyncratic.) Agranulocytosis and aplastic anemia have been reported. These cases rarely were fatal. Rare cases of thrombocytopenic purpura have been reported.
Other
Exacerbation of porphyric symptoms.

OVERDOSAGE

Suicidal attempts with meprobamate have resulted in drowsiness, lethargy, stupor, ataxia, coma, shock, vasomotor, and respiratory collapse. Some suicidal attempts have been fatal.
The following data on meprobamate tablets have been reported in the literature and from other sources. These data are not expected to correlate with each case (considering factors such as individual susceptibility and length of time from ingestion to treatment), but represent the usual ranges reported.
Acute simple overdose (meprobamate alone): Death has been reported with ingestion of as little as 12 g meprobamate and survival with as much as 40 g.
Blood Levels
0.5-2 mg% represents the usual blood level range of meprobamate after therapeutic doses. The level may occasionally be as high as 3 mg%.
3-10 mg% usually corresponds to findings of mild to moderate symptoms of overdosage, such as stupor or light coma.
10-20 mg% usually corresponds to deeper coma, requiring more intensive treatment. Some fatalities occur.
At levels greater than 20 mg%, more fatalities than survivals can be expected.
Acute combined overdose(meprobamate with alcohol or other CNS depressants or psychotropic drugs): Since effects can be additive, a history of ingestion of a low dose of meprobamate plus any of these compounds (or of a relative low blood or tissue level) cannot be used as a prognostic indicator.
In cases where excessive doses have been taken, sleep ensues rapidly and blood pressure, pulse, and respiratory rates are reduced to basal levels. Any drug remaining in the stomach should be removed and symptomatic therapy given. Should respiration or blood pressure become compromised, respiratory assistance, central nervous system stimulants, and pressor agents should be administered cautiously as indicated. Meprobamate is metabolized in the liver and excreted by the kidney. Diuresis, osmotic (mannitol) diuresis, peritoneal dialysis, and hemodialysis have been used successfully. Careful monitoring of urinary output is necessary and caution should be taken to avoid overhydration. Relapse and death, after initial recovery, have been attributed to incomplete gastric emptying and delayed absorption. Meprobamate can be measured in biological fluids by two methods: colorimetric (Hoffman, A.J. and Ludwig, B.J.: J Amer Pharm Assn 48: 740, 1959) and gas chromatographic (Douglas, J.F. et al: Anal Chem 39: 956, 1967).

DOSAGE & ADMINISTRATION

Meprobamate Tablets USP: The usual adult daily dosage is 1200mg to 1600 mg, in three or four divided doses; a daily dosage above 2400 mg is not recommended. The usual daily dosage for children ages six to twelve years is 200 mg to 600 mg, in two or three divided doses.
Not recommended for children under age 6 (see Usage in Children).

HOW SUPPLIED

Meprobamate Tablets USP 200 mg are white to off white, round, biconvex, uncoated tablets debossed with “L125” on one side and break line on other side.
NDC 46708-019-30 Bottle of 30
NDC 46708-019-71 Bottle of 100
NDC 46708-019-91 Bottle of 1000
Meprobamate Tablets USP 400 mg are white to off white, round, biconvex, uncoated tablets debossed with “L105” on one side and break line on other side.
NDC 46708-020-30 Bottle of 30
NDC 46708-020-71 Bottle of 100
NDC 46708-020-91 Bottle of 1000
Dispense in well-closed container with child-resistant closure.
Store at controlled room temperature, excursions permitted to 15°C-30°C (59°F-86°F).
Preserve in well closed container.
Call your doctor for medical advice about side effects. You may report side effects to FDA at 1-800-FDA-1088.
Manufactured by:

Alembic Pharmaceuticals Limited (Formulation Division),

Village Panelav, P. O. Tajpura, Near Baska,

Taluka-Halol, Panchmahal, Gujarat, India.

Revision Date: 07/2013

PACKAGE LABEL.PRINCIPAL DISPLAY PANEL

Meprobamate Tablets USP, 200 mg (30 Tablets in 1 HDPE Bottle)
Each uncoated tablet contains: Meprobamate, USP.......... 200 mg
46708-019-30

Meprobamate Tablets USP, 400 mg (30 Tablets in 1 HDPE Bottle)
Each uncoated tablet contains: Meprobamate, USP.......... 400 mg
46708-020-30